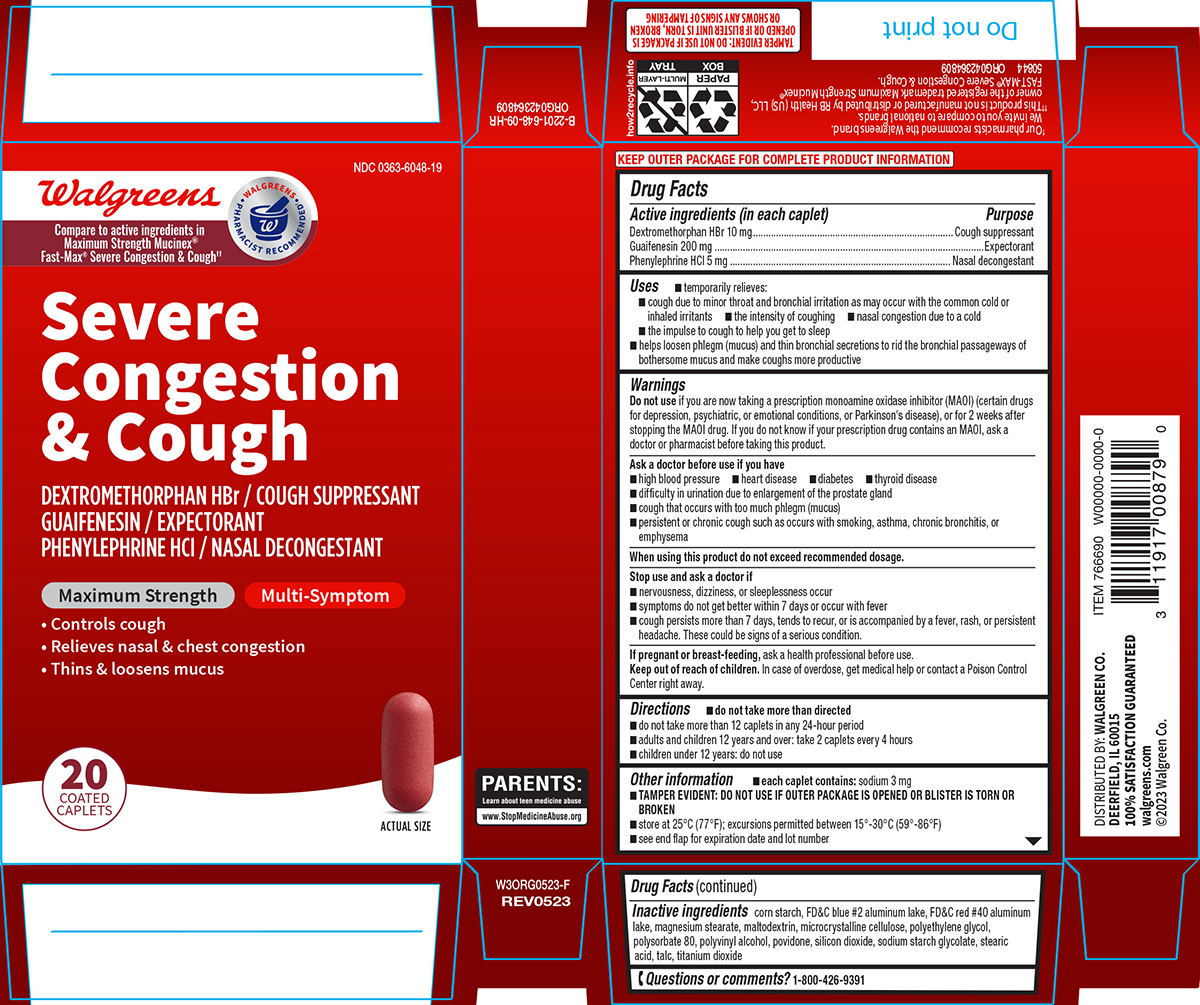 DRUG LABEL: Severe Congestion and Cough
NDC: 0363-6048 | Form: TABLET, FILM COATED
Manufacturer: Walgreen Company
Category: otc | Type: HUMAN OTC DRUG LABEL
Date: 20250722

ACTIVE INGREDIENTS: DEXTROMETHORPHAN HYDROBROMIDE 10 mg/1 1; GUAIFENESIN 200 mg/1 1; PHENYLEPHRINE HYDROCHLORIDE 5 mg/1 1
INACTIVE INGREDIENTS: STARCH, CORN; FD&C BLUE NO. 2--ALUMINUM LAKE; FD&C RED NO. 40; MAGNESIUM STEARATE; MALTODEXTRIN; MICROCRYSTALLINE CELLULOSE; POLYETHYLENE GLYCOL, UNSPECIFIED; POLYSORBATE 80; POLYVINYL ALCOHOL, UNSPECIFIED; POVIDONE, UNSPECIFIED; SILICON DIOXIDE; SODIUM STARCH GLYCOLATE TYPE A POTATO; STEARIC ACID; TALC; TITANIUM DIOXIDE

Walgreens 44-648-SCC

Active ingredients (in each caplet)

Dextromethorphan HBr 10 mg
Guaifenesin 200 mg
Phenylephrine HCl 5 mg

Purpose

Cough suppressant
Expectorant
Nasal decongestant

Uses

- temporarily relieves:
  - cough due to minor throat and bronchial irritation as may occur with the common cold or inhaled irritants
  - the intensity of coughing
  - the impulse to cough to help you get to sleep
  - nasal congestion due to a cold
- helps loosen phlegm (mucus) and thin bronchial secretions to rid the bronchial passageways of bothersome mucus and make coughs more productive

Warnings

Do not use

if you are now taking a prescription monoamine oxidase inhibitor (MAOI) (certain drugs for depression, psychiatric, or emotional conditions, or Parkinson's disease), or for 2 weeks after stopping the MAOI drug. If you do not know if your prescription drug contains an MAOI, ask a doctor or pharmacist before taking this product.

Ask a doctor before use if you have

- high blood pressure
- heart disease
- difficulty in urination due to enlargement of the prostate gland
- diabetes
- thyroid disease
- persistent or chronic cough such as occurs with smoking, asthma, chronic bronchitis, or emphysema
- cough that occurs with too much phlegm (mucus)

When using this product

do not exceed recommended dosage.

Stop use and ask a doctor if

- nervousness, dizziness, or sleeplessness occur
- symptoms do not get better within 7 days or occur with fever
- cough persists more than 7 days, tends to recur, or is accompanied by a fever, rash, or persistent headache.

These could be signs of a serious condition.

If pregnant or breast-feeding,

ask a health professional before use.

Keep out of reach of children.

In case of overdose, get medical help or contact a Poison Control Center right away.

Directions

- do not take more than directed
- do not take more than 12 caplets in any 24-hour period
- adults and children 12 years and over: take 2 caplets every 4 hours
- children under 12 years: do not use

Other information

- each caplet contains: sodium 3 mg
- TAMPER EVIDENT: DO NOT USE IF OUTER PACKAGE IS OPENED OR BLISTER IS TORN OR BROKEN
- store at 25°C (77°F); excursions permitted between 15°-30°C (59°-86°F)
- see end flap for expiration date and lot number

Inactive ingredients

corn starch, FD&C blue #2 aluminum lake, FD&C red #40 aluminum lake, magnesium stearate, maltodextrin, microcrystalline cellulose, polyethylene glycol, polysorbate 80, polyvinyl alcohol, povidone, silicon dioxide, sodium starch glycolate, stearic acid, talc, titanium dioxide

Questions or comments?

1-800-426-9391

Principal display panel

NDC 0363-6048-19

Walgreens

WALGREENS PHARMACIST RECOMMENDED†

Compare to active ingredients in
Maximum Strength Mucinex®
Fast-Max® Severe Congestion & Cough††

Severe
Congestion
& Cough

DEXTROMETHORPHAN HBr / COUGH SUPPRESSANT
GUAIFENESIN / EXPECTORANT
PHENYLEPHRINE HCl / NASAL DECONGESTANT

Maximum Strength

Multi-Symptom

• Controls cough
• Relieves nasal & chest congestion
• Thins & loosens mucus

20
COATED
CAPLETS

ACTUAL SIZE

TAMPER EVIDENT: DO NOT USE IF PACKAGE IS
OPENED OR IF BLISTER UNIT IS TORN, BROKEN
OR SHOWS ANY SIGNS OF TAMPERING

DISTRIBUTED BY: WALGREEN CO.
DEERFIELD, IL 60015
100% SATISFACTION GUARANTEED
walgreens.com
©2023 Walgreen Co.

†Our pharmacists recommend the Walgreens brand.
We invite you to compare to national brands.
††This product is not manufactured or distributed by RB Health (US) LLC,
owner of the registered trademark Maximum Strength Mucinex®
FAST-MAX® Severe Congestion & Cough.

50844 ORG042364809

Walgreens 44-648